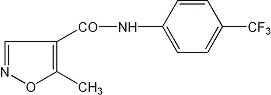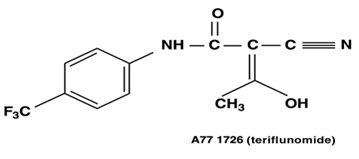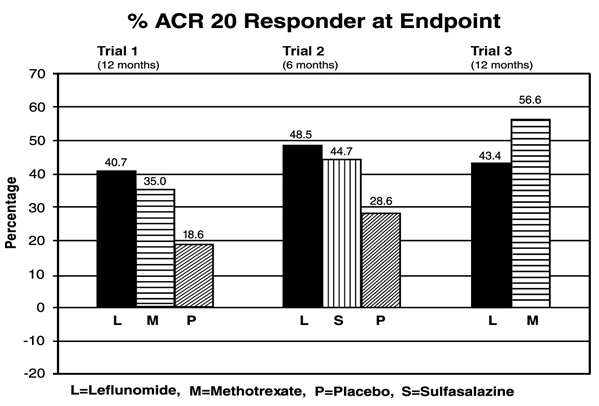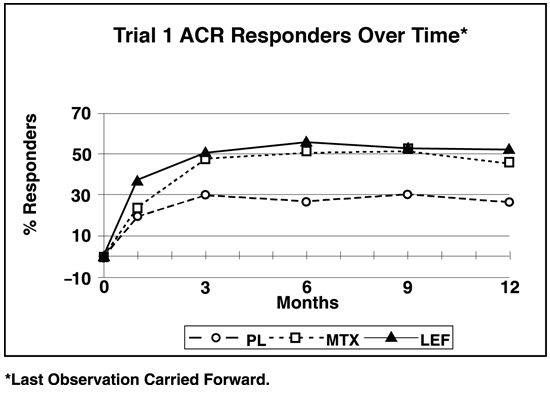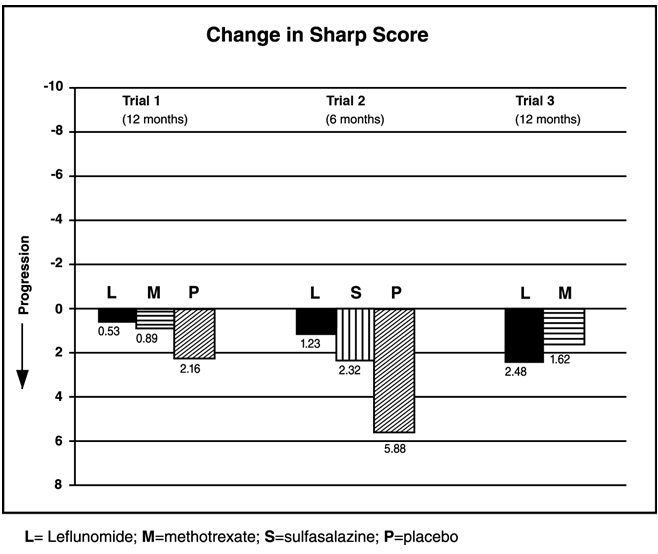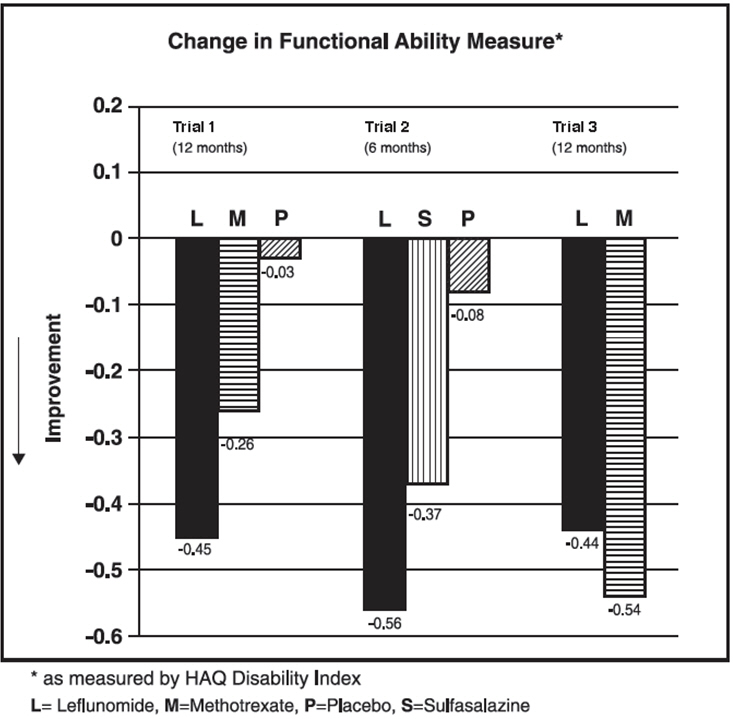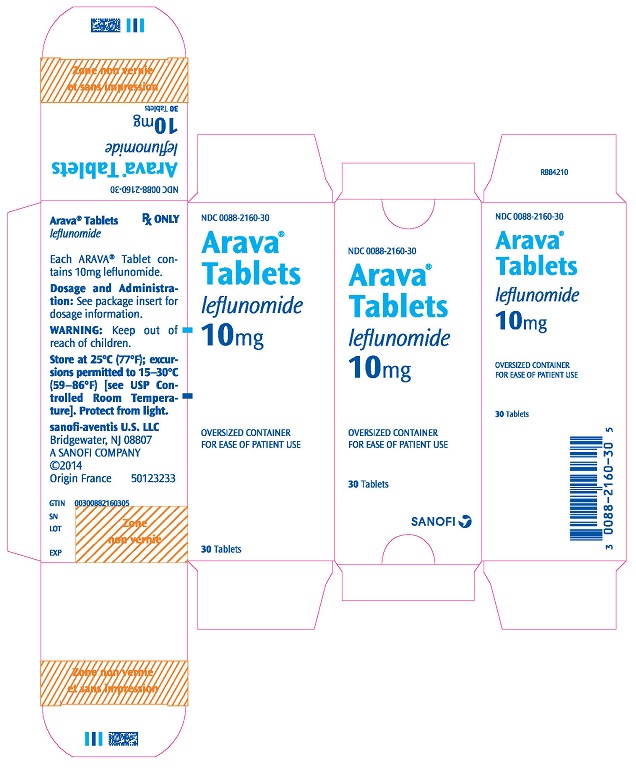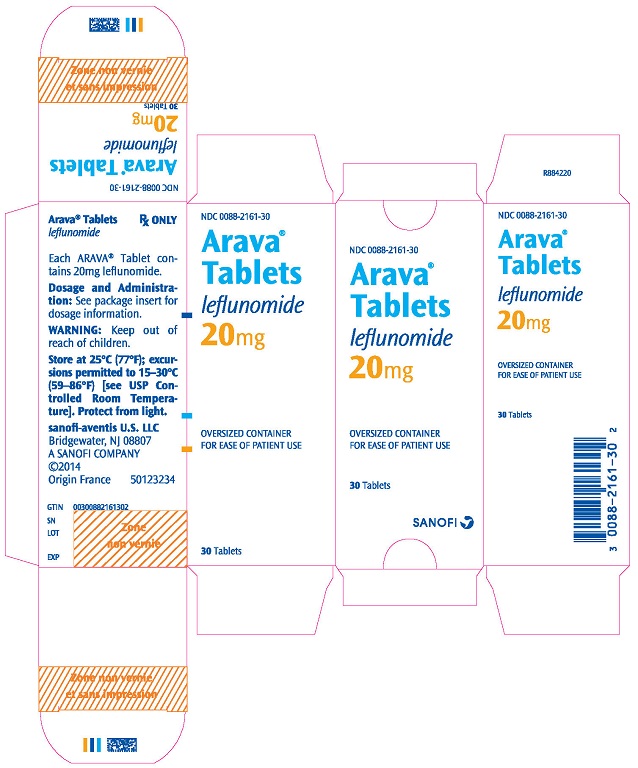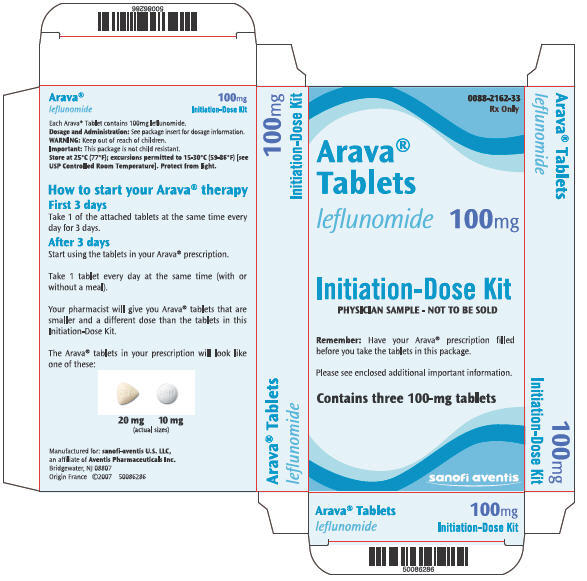 DRUG LABEL: Arava
NDC: 0088-2160 | Form: TABLET, FILM COATED
Manufacturer: sanofi-aventis U.S. LLC
Category: prescription | Type: HUMAN PRESCRIPTION DRUG LABEL
Date: 20250604

ACTIVE INGREDIENTS: LEFLUNOMIDE 10 mg/1 1
INACTIVE INGREDIENTS: SILICON DIOXIDE; CROSPOVIDONE (120 .MU.M); HYPROMELLOSE, UNSPECIFIED; LACTOSE MONOHYDRATE; MAGNESIUM STEARATE; POLYETHYLENE GLYCOL, UNSPECIFIED; POVIDONE, UNSPECIFIED; TALC; TITANIUM DIOXIDE; STARCH, CORN

HIGHLIGHTS OF PRESCRIBING INFORMATION

These highlights do not include all the information needed to use ARAVA safely and effectively. See full prescribing information for ARAVA.
ARAVA (leflunomide) tablets, for oral use
Initial U.S. Approval: 1998

WARNING: EMBRYO-FETAL TOXICITY and HEPATOTOXICITY

See full prescribing information for complete boxed warning.

Embryo-Fetal Toxicity

- Teratogenicity and embryo-lethality occurred in animals administered leflunomide. (5.1, 8.1)
- Exclude pregnancy prior to initiating ARAVA therapy. (5.1, 8.3)
- Advise use of effective contraception in females of reproductive potential during treatment and during a drug elimination procedure. (5.1, 5.3, 8.3)
- Stop ARAVA and use an accelerated drug elimination procedure if the patient becomes pregnant. (5.1, 5.3, 8.1)

Hepatotoxicity

- Severe liver injury and fatal liver failure have been reported. (5.2)
- Avoid ARAVA use in patients with pre-existing liver disease, or those with serum alanine aminotransferase (ALT) >2 × ULN. (5.2, 8.6)
- Use caution when ARAVA is given with other potentially hepatotoxic drugs. (5.2)
- Monitor ALT levels. Interrupt ARAVA treatment if ALT elevation >3-fold ULN. If likely leflunomide-induced, start accelerated drug elimination procedure and monitor liver tests weekly until normalized. (5.2, 5.3)

RECENT MAJOR CHANGES

Warnings and Precautions, Skin Ulcers (5.6) | 6/2024

1 INDICATIONS AND USAGE

ARAVA is a pyrimidine synthesis inhibitor indicated for the treatment of adults with active rheumatoid arthritis. (1)

2 DOSAGE AND ADMINISTRATION

- Loading dosage for patients at low risk for ARAVA-associated hepatotoxicity and ARAVA-associated myelosuppression: 100 mg daily for 3 days. (2.1)
- Maintenance dosage: 20 mg daily. (2.1)
  - Maximum recommended daily dosage: 20 mg once daily. (2.1)
  - If 20 mg once daily is not tolerated, may decrease dosage to 10 mg once daily. (2.1)
- Screen patients for active and latent tuberculosis, pregnancy test (females), blood pressure, and laboratory tests before starting ARAVA. (2.2)

3 DOSAGE FORMS AND STRENGTHS

Tablets: 10 mg, 20 mg, 100 mg. (3)

4 CONTRAINDICATIONS

- Pregnancy. (4, 5.1, 8.1)
- Severe hepatic impairment. (4, 5.2)
- Hypersensitivity to ARAVA or any of its inactive components. (4)
- Current teriflunomide treatment. (4)

5 WARNINGS AND PRECAUTIONS

- After stopping ARAVA, it is recommended that an accelerated drug elimination procedure be used to reduce the plasma concentrations of the active metabolite, teriflunomide. (5.3)
- Severe infections (including sepsis), pancytopenia, agranulocytosis, and thrombocytopenia: Stop ARAVA and use accelerated elimination procedure. Do not start ARAVA in patients with active infection. Monitor CBCs during treatment with ARAVA. (5.4)
- Stevens-Johnson syndrome and toxic epidermal necrolysis, drug reaction with eosinophilia and systemic symptoms (DRESS): Stop ARAVA and use accelerated elimination procedure. (5.5)
- Skin ulcers: If skin ulcer is suspected, discontinue leflunomide treatment and consider an accelerated drug elimination procedure. (5.6)
- Peripheral neuropathy: If patient develops symptoms consistent with peripheral neuropathy, evaluate patient and consider discontinuing ARAVA. (5.8)
- Interstitial lung disease: May be fatal. New onset or worsening symptoms may necessitate discontinuation of ARAVA and initiation of accelerated elimination procedure. (5.9)
- Increased blood pressure: Monitor and treat. (5.11)

6 ADVERSE REACTIONS

- The most commonly reported adverse reactions (≥10%) regardless of relation to ARAVA treatment were diarrhea, respiratory infection, nausea, headache, rash, abnormal liver enzymes, and dyspepsia. (6.1)

To report SUSPECTED ADVERSE REACTIONS, contact sanofi-aventis U.S. LLC at 1-800-633-1610 or FDA at 1-800-FDA-1088 or www.fda.gov/medwatch.

7 DRUG INTERACTIONS

- Drugs metabolized by CYP2C8 and OAT3 transporters: Monitor patients because teriflunomide may increase exposure of these drugs. (7)
- Teriflunomide may increase exposure of ethinylestradiol and levonorgestrel. Choose an appropriate oral contraceptive. (7)
- Drugs metabolized by CYP1A2: Monitor patients because teriflunomide may decrease exposure of these drugs. (7)
- Warfarin: Monitor INR as teriflunomide may decrease INR. (7)
- Drugs metabolized by BCRP and OATP1B1/B3 transporters: Monitor patients because teriflunomide may increase exposure of these drugs. (7)
- Rosuvastatin: The dose of rosuvastatin should not exceed 10 mg once daily in patients taking ARAVA. (7)

8 USE IN SPECIFIC POPULATIONS

- Lactation: Discontinue breastfeeding. (8.2)
- Females and Males of Reproductive Potential: See FPI for information regarding contraception. (8.3)
- Safety and effectiveness in pediatric patients <12 years of age have not been established. (8.4)

FULL PRESCRIBING INFORMATION

WARNING: EMBRYO-FETAL TOXICITY and HEPATOTOXICITY

Embryo-Fetal Toxicity

ARAVA is contraindicated for use in pregnant women because of the potential for fetal harm. Teratogenicity and embryo-lethality occurred in animals administered leflunomide at doses lower than the human exposure level. Exclude pregnancy before the start of treatment with ARAVA in females of reproductive potential. Advise females of reproductive potential to use effective contraception during ARAVA treatment and during an accelerated drug elimination procedure after ARAVA treatment. Stop ARAVA and use an accelerated drug elimination procedure if the patient becomes pregnant [see Contraindications (4), Warnings and Precautions (5.1, 5.3), Use in Specific Populations (8.1, 8.3)], and Clinical Pharmacology (12.3)].

Hepatotoxicity

Severe liver injury, including fatal liver failure, has been reported in patients treated with ARAVA. ARAVA is contraindicated in patients with severe hepatic impairment. Concomitant use of ARAVA with other potentially hepatotoxic drugs may increase the risk of liver injury. Patients with pre-existing acute or chronic liver disease, or those with serum alanine aminotransferase (ALT) >2 × ULN before initiating treatment, are at increased risk and should not be treated with ARAVA. Monitor ALT levels at least monthly for six months after starting ARAVA, and thereafter every 6 to 8 weeks. If leflunomide-induced liver injury is suspected, stop ARAVA treatment, start an accelerated drug elimination procedure, and monitor liver tests weekly until normalized [see Contraindications (4), Warnings and Precautions (5.2, 5.3), Use in Specific Populations (8.6)].

1 INDICATIONS AND USAGE

ARAVA is indicated for the treatment of adults with active rheumatoid arthritis (RA).

2 DOSAGE AND ADMINISTRATION

2.1 Recommended Dosage

The recommended dosage of ARAVA is 20 mg once daily. Treatment may be initiated with or without a loading dose, depending upon the patient's risk of ARAVA-associated hepatotoxicity and ARAVA-associated myelosuppression. The loading dose provides steady-state concentrations more rapidly.

- For patients who are at low risk for ARAVA-associated hepatotoxicity and ARAVA-associated myelosuppression, the recommended ARAVA loading dose is 100 mg once daily for 3 days. Subsequently administer 20 mg once daily.
- For patients at high risk for ARAVA-associated hepatotoxicity (e.g., those taking concomitant methotrexate) or ARAVA-associated myelosuppression (e.g., patients taking concomitant immunosuppressants), the recommended ARAVA dosage is 20 mg once daily without a loading dose [see Warnings and Precautions (5.2, 5.4)].

The maximum recommended daily dose is 20 mg once per day. Consider dosage reduction to 10 mg once daily for patients who are not able to tolerate 20 mg daily (i.e., for patients who experience any adverse events listed in Table 1).

Monitor patients carefully after dosage reduction and after stopping therapy with ARAVA, since the active metabolite of leflunomide, teriflunomide, is slowly eliminated from the plasma [see Clinical Pharmacology (12.3)]. After stopping ARAVA treatment, an accelerated drug elimination procedure is recommended to reduce the plasma concentrations of the active metabolite, teriflunomide [see Warnings and Precautions (5.3)]. Without use of an accelerated drug elimination procedure, it may take up to 2 years to reach undetectable plasma teriflunomide concentrations after stopping ARAVA [see Clinical Pharmacology (12.3)].

2.2 Evaluation and Testing Prior to Starting ARAVA

Prior to starting ARAVA treatment, the following evaluations and tests are recommended:

- Evaluate patients for active tuberculosis and screen patients for latent tuberculosis infection [see Warnings and Precautions (5.4)]
- Laboratory tests including serum alanine aminotransferase (ALT); and white blood cell, hemoglobin or hematocrit, and platelet counts [see Warnings and Precautions (5.2, 5.4)]
- For females of reproductive potential, pregnancy testing [see Warnings and Precautions (5.1)]
- Check blood pressure [see Warnings and Precautions (5.11)]

3 DOSAGE FORMS AND STRENGTHS

ARAVA Tablets are available in three strengths:

- Tablets: 10 mg, supplied as white, round film-coated tablet embossed with "ZBN" on one side
- Tablets: 20 mg, supplied as light-yellow, triangular film-coated tablet embossed with "ZBO" on one side
- Tablets: 100 mg, supplied as white, round film-coated tablet embossed with "ZBP" on one side

4 CONTRAINDICATIONS

ARAVA is contraindicated in:

- Pregnant women. ARAVA may cause fetal harm. If a woman becomes pregnant while taking this drug, stop ARAVA, apprise the patient of the potential hazard to the fetus, and begin a drug elimination procedure [see Warnings and Precautions (5.1, 5.3) and Use in Specific Populations (8.1)].
- Patients with severe hepatic impairment [see Warnings and Precautions (5.2)].
- Patients with known hypersensitivity to leflunomide or any of the other components of ARAVA. Known reactions include anaphylaxis [see Adverse Reactions (6.1)].
- Patients being treated with teriflunomide [see Drug Interactions (7)].

5 WARNINGS AND PRECAUTIONS

5.1 Embryo-Fetal Toxicity

ARAVA may cause fetal harm when administered to a pregnant woman. Teratogenicity and embryo-lethality occurred in animal reproduction studies with leflunomide at doses lower than the human exposure level [see Use in Specific Populations (8.1)].

ARAVA is contraindicated for use in pregnant women [see Contraindications (4)]. Exclude pregnancy before starting treatment with ARAVA in females of reproductive potential [see Dosage and Administration (2.2)]. Advise females of reproductive potential to use effective contraception during ARAVA treatment and during an accelerated drug elimination procedure after ARAVA treatment [see Use in Specific Populations (8.3)]. If a woman becomes pregnant while taking ARAVA, stop treatment with ARAVA, apprise the patient of the potential risk to a fetus, and perform an accelerated drug elimination procedure to achieve nondetectable plasma concentrations of teriflunomide, the active metabolite of leflunomide [see Warnings and Precautions (5.3)].

Upon discontinuing ARAVA, it is recommended that all females of reproductive potential undergo an accelerated drug elimination procedure. Women receiving ARAVA treatment who wish to become pregnant must discontinue ARAVA and undergo an accelerated drug elimination procedure, which includes verification that plasma concentrations of the active metabolite of leflunomide, teriflunomide, are less than 0.02 mg/L (0.02 mcg/mL). Based on animal data, human plasma concentrations of teriflunomide of less than 0.02 mg/L (0.02 mcg/mL) are expected to have minimal embryo-fetal risk [see Contraindications (4), Warnings and Precautions (5.3), and Use in Specific Populations (8.1)].

5.2 Hepatotoxicity

Severe liver injury, including fatal liver failure, has been reported in some patients treated with ARAVA. Patients with pre-existing acute or chronic liver disease, or those with serum alanine aminotransferase (ALT) of greater than twice the upper limits of normal (>2 × ULN) before initiating treatment, should not be treated with ARAVA. Use caution when ARAVA is given with other potentially hepatotoxic drugs. Monitoring of ALT levels is recommended at least monthly for six months after starting ARAVA, and thereafter every 6 to 8 weeks. If ALT elevation >3-fold ULN occurs, interrupt ARAVA therapy and investigate the cause. If likely ARAVA-induced, perform the accelerated drug elimination procedure and monitor liver tests weekly until normalized [see Warnings and Precautions (5.3)]. If ARAVA-induced liver injury is unlikely because some other cause has been found, resumption of ARAVA therapy may be considered.

If ARAVA and methotrexate are given concomitantly, follow the American College of Rheumatology (ACR) guidelines for monitoring methotrexate liver toxicity with ALT, AST, and serum albumin testing.

5.3 Procedure for Accelerated Elimination of ARAVA and its Active Metabolite

The active metabolite of leflunomide, teriflunomide, is eliminated slowly from the plasma [see Clinical Pharmacology (12.3)].

Use of an accelerated drug elimination procedure will rapidly reduce plasma concentrations of leflunomide and its active metabolite, teriflunomide. Therefore, an accelerated elimination procedure should be considered at any time after discontinuation of ARAVA, and in particular, when a patient has experienced a severe adverse reaction (e.g., hepatotoxicity, serious infection, bone marrow suppression, Stevens-Johnson Syndrome, toxic epidermal necrolysis, peripheral neuropathy, interstitial lung disease), suspected hypersensitivity, or has become pregnant. It is recommended that all women of childbearing potential undergo an accelerated elimination procedure after stopping ARAVA treatment.

Without use of an accelerated drug elimination procedure, it may take up to 2 years to reach plasma teriflunomide concentrations of less than 0.02 mg/L, the plasma concentration not associated with embryo-fetal toxicity in animals.

Elimination can be accelerated by the following procedures:

1. Administer cholestyramine 8 grams orally 3 times daily for 11 days.
2. Alternatively, administer 50 grams of activated charcoal powder (made into a suspension) orally every 12 hours for 11 days.

Verify plasma teriflunomide concentrations of less than 0.02 mg/L (0.02 µg/mL) by two separate tests at least 14 days apart. If plasma teriflunomide concentrations are higher than 0.02 mg/L, repeat cholestyramine and/or activated charcoal treatment.

The duration of accelerated drug elimination treatment may be modified based on the clinical status and tolerability of the elimination procedure. The procedure may be repeated as needed, based on teriflunomide concentrations and clinical status.

Use of the accelerated drug elimination procedure may potentially result in return of disease activity if the patient had been responding to ARAVA treatment.

5.4 Immunosuppression, Bone Marrow Suppression, and Risk of Serious Infections

ARAVA is not recommended for patients with severe immunodeficiency, bone marrow dysplasia, or severe, uncontrolled infections. If a serious infection occurs, consider interrupting ARAVA therapy and initiating the accelerated drug elimination procedure [see Warnings and Precautions (5.3)]. Medications like ARAVA that have immunosuppression potential may cause patients to be more susceptible to infections, including opportunistic infections, especially Pneumocystis jirovecii pneumonia, tuberculosis (including extra-pulmonary tuberculosis), and aspergillosis. Severe infections including sepsis, which may be fatal, have been reported in patients receiving ARAVA, especially Pneumocystis jirovecii pneumonia and aspergillosis. Most of the reports were confounded by concomitant immunosuppressant therapy and/or comorbid illness which, in addition to rheumatoid arthritis, may predispose patients to infection.

Cases of tuberculosis were observed in clinical studies with teriflunomide, the metabolite of ARAVA. Prior to initiating ARAVA, all patients should be screened for active and inactive ("latent") tuberculosis infection as per commonly used diagnostic tests. ARAVA has not been studied in patients with a positive tuberculosis screen, and the safety of ARAVA in individuals with latent tuberculosis infection is unknown. Patients testing positive in tuberculosis screening should be treated by standard medical practice prior to therapy with ARAVA and monitored carefully during ARAVA treatment for possible reactivation of the infection.

Pancytopenia, agranulocytosis, and thrombocytopenia have been reported in patients receiving ARAVA alone. These events have been reported most frequently in patients who received concomitant treatment with methotrexate or other immunosuppressive agents, or who had recently discontinued these therapies; in some cases, patients had a prior history of a significant hematologic abnormality.

Patients taking ARAVA should have platelet, white blood cell count and hemoglobin or hematocrit monitored at baseline and monthly for six months following initiation of therapy and every 6 to 8 weeks thereafter. If used with concomitant methotrexate and/or other potential immunosuppressive agents, chronic monitoring should be monthly. If evidence of bone marrow suppression occurs in a patient taking ARAVA, stop treatment with ARAVA and perform an accelerated drug elimination procedure to reduce the plasma concentration of the ARAVA active metabolite, teriflunomide [see Warnings and Precautions (5.3)].

In any situation in which the decision is made to switch from ARAVA to another antirheumatic agent with a known potential for hematologic suppression, it would be prudent to monitor for hematologic toxicity, because there will be overlap of systemic exposure to both compounds.

5.5 Stevens-Johnson Syndrome, Toxic Epidermal Necrolysis, and Drug Reactions with Eosinophilia and Systemic Symptoms

Rare cases of Stevens-Johnson syndrome and toxic epidermal necrolysis, and drug reaction with eosinophilia and systemic symptoms (DRESS) have been reported in patients receiving ARAVA. If a patient taking ARAVA develops any of these conditions, stop ARAVA treatment and perform an accelerated drug elimination procedure [see Warnings and Precautions (5.3)].

5.6 Skin Ulcers

Skin ulcers may occur in patients during therapy with leflunomide. If leflunomide-associated skin ulcer is suspected or if skin ulcers persist despite appropriate therapy, leflunomide discontinuation and an accelerated drug elimination procedure should be considered [see Warnings and Precautions (5.3)]. The decision to resume leflunomide following skin ulcers should be based on clinical judgment of adequate wound healing.

5.7 Malignancy and Lymphoproliferative Disorders

The risk of malignancy, particularly lymphoproliferative disorders, is increased with the use of some immunosuppression medications. There is a potential for immunosuppression with ARAVA. No apparent increase in the incidence of malignancies and lymphoproliferative disorders was reported in the clinical trials of ARAVA, but larger dosages and longer-term studies would be needed to determine whether there is an increased risk of malignancy or lymphoproliferative disorders with ARAVA.

5.8 Peripheral Neuropathy

Cases of peripheral neuropathy have been reported in patients receiving ARAVA and in clinical studies with teriflunomide, the active metabolite of leflunomide. Most patients recovered after discontinuation of treatment, but some patients had persistent symptoms. Age older than 60 years, concomitant neurotoxic medications, and diabetes may increase the risk for peripheral neuropathy. If a patient taking ARAVA develops a peripheral neuropathy, consider discontinuing ARAVA therapy and performing an accelerated drug elimination procedure [see Warnings and Precautions (5.3)].

5.9 Interstitial Lung Disease

Interstitial lung disease and worsening of pre-existing interstitial lung disease have been reported during treatment with ARAVA and has been associated with fatal outcomes [see Adverse Reactions (6.2)]. The risk of ARAVA-associated interstitial lung disease is increased in patients with a history of interstitial lung disease. Interstitial lung disease is a potentially fatal disorder that may occur acutely at any time during therapy and has a variable clinical presentation. New onset or worsening pulmonary symptoms, such as cough and dyspnea, with or without associated fever, may be a reason for discontinuation of ARAVA therapy and for further investigation as appropriate. If discontinuation of ARAVA is necessary, consider performing an accelerated drug elimination procedure [see Warnings and Precautions (5.3)].

5.10 Vaccinations

No clinical data are available on the efficacy and safety of vaccinations during ARAVA treatment. Vaccination with live vaccines is, however, not recommended. The long half-life of the active metabolite of ARAVA should be considered when contemplating administration of a live vaccine after stopping ARAVA.

5.11 Blood Pressure Monitoring

In placebo-controlled studies with the active metabolite of ARAVA, teriflunomide, elevations in blood pressure were observed in some subjects. Blood pressure should be checked before starting treatment with ARAVA and monitored periodically thereafter [see Adverse Reactions (6.1)].

6 ADVERSE REACTIONS

The following serious adverse reactions are described elsewhere in the labeling:

- Hepatotoxicity [see Warnings and Precautions (5.2)]
- Immunosuppression [see Warnings and Precautions (5.4)]
- Bone marrow suppression [see Warnings and Precautions (5.4)]
- Serious infections [see Warnings and Precautions (5.4)]
- Stevens-Johnson syndrome, toxic epidermal necrolysis, and drug reactions with eosinophilia and systemic symptoms [see Warnings and Precautions (5.5)]
- Skin ulcers [see Warnings and Precautions (5.6)]
- Peripheral neuropathy [see Warnings and Precautions (5.8)]
- Interstitial lung disease [see Warnings and Precautions (5.9)]

6.1 Clinical Trials Experience

Because clinical studies are conducted under widely varying conditions, adverse reaction rates observed in the clinical studies of a drug cannot be directly compared to rates in the clinical studies of another drug and may not reflect the rates observed in practice.

In clinical studies (Trials 1, 2, and 3), 1,865 patients were treated with ARAVA administered as either monotherapy or in combination with methotrexate or sulfasalazine. Patients ranged in age from 19 to 85 years, with an overall median age of 58 years. The mean duration of RA was 6 years ranging from 0 to 45 years.

Elevation of Liver Enzymes

Treatment with ARAVA was associated with elevations of liver enzymes, primarily ALT and AST, in a significant number of patients; these effects were generally reversible. Most transaminase elevations were mild (≤2-fold ULN) and usually resolved while continuing treatment. Marked elevations (>3-fold ULN) occurred infrequently and reversed with dose reduction or discontinuation of treatment. Table 1 shows liver enzyme elevations seen with monthly monitoring in clinical trials Trial 1 and Trial 2. It was notable that the absence of folate use in Trial 3 was associated with a considerably greater incidence of liver enzyme elevation on methotrexate.

Table 1: Liver Enzyme Elevations >3-fold Upper Limits of Normal (ULN) in Patients with RA in Trials 1, 2, and 3 [Only 10% of patients in Trial 3 received folate. All patients in Trial 1 received folate.]
 | Trial 1 |  |  | Trial 2 |  |  | Trial 3
 | ARAVA | PL | MTX | ARAVA | PL | SSZ | ARAVA | MTX
 | 20 mg/day (n=182) | (n=118) | 7.5–15 mg/wk (n=182) | 20 mg/day (n=133) | (n=92) | 2 g/day (n=133) | 20 mg/day (n=501) | 7.5–15 mg/wk (n=498)
ALT (SGPT)
>3-fold ULN (n %) | 8(4.4) | 3(2.5) | 5(2.7) | 2(1.5) | 1(1.1) | 2(1.5) | 13(2.6) | 83 (16.7)
Reversed to ≤2-fold ULN: | 8 | 3 | 5 | 2 | 1 | 2 | 12 | 82
Timing of Elevation
0–3 Months | 6 | 1 | 1 | 2 | 1 | 2 | 7 | 27
4–6 Months | 1 | 1 | 3 | - | - | - | 1 | 34
7–9 Months | 1 | 1 | 1 | - | - | - | - | 16
10–12 Months | - | - | - | - | - | - | 5 | 6
MTX = methotrexate, PL = placebo, SSZ = sulfasalazine, ULN = Upper limit of normal

In a 6-month study of 263 patients with persistent active rheumatoid arthritis despite methotrexate therapy, and with normal LFTs, ARAVA was administered to a group of 130 patients starting at 10 mg per day and increased to 20 mg as needed. An increase in ALT greater than or equal to three times the ULN was observed in 3.8% of patients compared to 0.8% in 133 patients continued on methotrexate with placebo.

Most Common Adverse Reactions

The most common adverse reactions in ARAVA-treated patients with RA include diarrhea, elevated liver enzymes (ALT and AST), alopecia, and rash. Table 2 displays the most common adverse reactions in the controlled studies in patients with RA at one year (≥5% in any ARAVA treatment group).

Table 2: Percentage Of Patients With Adverse Events ≥5% In Any ARAVA Treated Group in all RA Studies in Patients with RA
 | Placebo-Controlled Trials |  |  |  | Active-Controlled Trials |  | All RA Studies
 | Trial 1 and 2 |  |  |  | Trial 3 [Only 10% of patients in Trial 3 received folate. All patients in Trial 1 received folate; none in Trial 2 received folate.]
 | ARAVA 20 mg/day (n=315) | PL (n=210) | SSZ 2 g/day (n=133) | MTX 7.5–15 mg/wk (n=182) | ARAVA 20 mg/day (n=501) | MTX 7.5–15 mg/wk (n=498) | ARAVA (n=1339) [Includes all controlled and uncontrolled trials with ARAVA (duration up to 12 months).]
Diarrhea | 27% | 12% | 10% | 20% | 22% | 10% | 17%
Headache | 13% | 11% | 12% | 21% | 10% | 8% | 7%
Nausea | 13% | 11% | 19% | 18% | 13% | 18% | 9%
Rash | 12% | 7% | 11% | 9% | 11% | 10% | 10%
Abnormal Liver Enzymes | 10% | 2% | 4% | 10% | 6% | 17% | 5%
Alopecia | 9% | 1% | 6% | 6% | 17% | 10% | 10%
Hypertension [Hypertension as a preexisting condition was overrepresented in all ARAVA treatment groups in phase III trials.] | 9% | 4% | 4% | 3% | 10% | 4% | 10%
Asthenia | 6% | 4% | 5% | 6% | 3% | 3% | 3%
Back Pain | 6% | 3% | 4% | 9% | 8% | 7% | 5%
GI/Abdominal Pain | 6% | 4% | 7% | 8% | 8% | 8% | 5%
Abdominal Pain | 5% | 4% | 4% | 8% | 6% | 4% | 6%
Allergic Reaction | 5% | 2% | 0% | 6% | 1% | 2% | 2%
Bronchitis | 5% | 2% | 4% | 7% | 8% | 7% | 7%
Dizziness | 5% | 3% | 6% | 5% | 7% | 6% | 4%
Mouth Ulcer | 5% | 4% | 3% | 10% | 3% | 6% | 3%
Pruritus | 5% | 2% | 3% | 2% | 6% | 2% | 4%
Rhinitis | 5% | 2% | 4% | 3% | 2% | 2% | 2%
Vomiting | 5% | 4% | 4% | 3% | 3% | 3% | 3%
Tenosynovitis | 2% | 0% | 1% | 2% | 5% | 1% | 3%
MTX = methotrexate, PL = placebo, SSZ = sulfasalazine

Adverse events during a second year of treatment with ARAVA in clinical trials were consistent with those observed during the first year of treatment and occurred at a similar or lower incidence.

Less Common Adverse Reactions

In addition, in controlled clinical trials, the following adverse events in the ARAVA treatment group occurred at a higher incidence than in the placebo group. These adverse events were deemed possibly related to the study drug.

Blood and Lymphatic System: leukocytosis, thrombocytopenia

Cardiovascular: chest pain, palpitation, thrombophlebitis of the leg, varicose vein

Eye: blurred vision, eye disorder, papilledema, retinal disorder, retinal hemorrhage

Gastrointestinal: alkaline phosphatase increased, anorexia, bilirubinemia, flatulence, gamma-GT increased, salivary gland enlarged, sore throat, vomiting, dry mouth

General Disorders: malaise

Immune System: anaphylactic reaction

Infection: abscess, flu syndrome, vaginal moniliasis

Nervous System: dizziness, headache, somnolence

Respiratory System: dyspnea

6.2 Postmarketing Experience

The following additional adverse reactions have been identified during postapproval use of ARAVA. Because these reactions are reported voluntarily from a population of uncertain size, it is not always possible to reliably estimate their frequency or establish a causal relationship to drug exposure.

Blood and Lymphatic System: agranulocytosis, leukopenia, neutropenia, pancytopenia

Infection: opportunistic infections, severe infections including sepsis

Gastrointestinal: acute hepatic necrosis, colitis, including microscopic colitis, hepatitis, jaundice/cholestasis, pancreatitis, severe liver injury such as hepatic failure

Immune System: angioedema

Nervous system: peripheral neuropathy

Respiratory: interstitial lung disease, including interstitial pneumonitis and pulmonary fibrosis, which may be fatal, pulmonary hypertension

Skin and Appendages: erythema multiforme, vasculitis including cutaneous necrotizing vasculitis, cutaneous lupus erythematosus, pustular psoriasis or worsening psoriasis

7 DRUG INTERACTIONS

Following oral administration, leflunomide is metabolized to an active metabolite, teriflunomide, which is responsible for essentially all of leflunomide's in vivo activity. Drug interaction studies have been conducted with both ARAVA (leflunomide) and with its active metabolite, teriflunomide, where the metabolite was directly administered to the test subjects.

Effect of Potent CYP and Transporter Inducers

Leflunomide is metabolized by CYP450 metabolizing enzymes. Concomitant use of ARAVA and rifampin, a potent inducer of CYP and transporters, increased the plasma concentration of teriflunomide by 40%. However, when coadministered with the metabolite, teriflunomide, rifampin did not affect its pharmacokinetics. No dosage adjustment is recommended for ARAVA when coadministered with rifampin. Because of the potential for ARAVA concentrations to continue to increase with multiple dosing, caution should be used if patients are to be receiving both ARAVA and rifampin [see Clinical Pharmacology (12.3)].

Effect on CYP2C8 Substrates

Teriflunomide is an inhibitor of CYP2C8 in vivo. In patients taking ARAVA, exposure of drugs metabolized by CYP2C8 (e.g., paclitaxel, pioglitazone, repaglinide, rosiglitazone) may be increased. Monitor these patients and adjust the dose of the concomitant drug(s) metabolized by CYP2C8 as required [see Clinical Pharmacology (12.3)].

Effect on Warfarin

Coadministration of ARAVA with warfarin requires close monitoring of the international normalized ratio (INR) because teriflunomide, the active metabolite of ARAVA, may decrease peak INR by approximately 25%.

Effect on Oral Contraceptives

Teriflunomide may increase the systemic exposures of ethinylestradiol and levonorgestrel. Consideration should be given to the type or dose of contraceptives used in combination with ARAVA [see Clinical Pharmacology (12.3)].

Effect on CYP1A2 Substrates

Teriflunomide, the active metabolite of ARAVA, may be a weak inducer of CYP1A2 in vivo. In patients taking ARAVA, exposure of drugs metabolized by CYP1A2 (e.g., alosetron, duloxetine, theophylline, tizanidine) may be reduced. Monitor these patients and adjust the dose of the concomitant drug(s) metabolized by CYP1A2 as required [see Clinical Pharmacology (12.3)].

Effect on Organic Anion Transporter 3 (OAT3) Substrates

Teriflunomide inhibits the activity of OAT3 in vivo. In patients taking ARAVA, exposure of drugs which are OAT3 substrates (e.g., cefaclor, cimetidine, ciprofloxacin, penicillin G, ketoprofen, furosemide, methotrexate, zidovudine) may be increased. Monitor these patients and adjust the dose of the concomitant drug(s) which are OAT3 substrates as required [see Clinical Pharmacology (12.3)].

Effect on BCRP and Organic Anion Transporting Polypeptide B1 and B3 (OATP1B1/1B3) Substrates

Teriflunomide inhibits the activity of BCRP and OATP1B1/1B3 in vivo. For a patient taking ARAVA, the dose of rosuvastatin should not exceed 10 mg once daily. For other substrates of BCRP (e.g., mitoxantrone) and drugs in the OATP family (e.g., methotrexate, rifampin), especially HMG-Co reductase inhibitors (e.g., atorvastatin, nateglinide, pravastatin, repaglinide, and simvastatin), consider reducing the dose of these drugs and monitor patients closely for signs and symptoms of increased exposures to the drugs while patients are taking ARAVA [see Clinical Pharmacology (12.3)].

8 USE IN SPECIFIC POPULATIONS

8.1 Pregnancy

Pregnancy Exposure Registry

There is a pregnancy exposure registry that monitors pregnancy outcomes in women exposed to ARAVA during pregnancy. Health care providers and patients are encouraged to report pregnancies by calling 1-877-311-8972 or visit http://www.pregnancystudies.org/participate-in-a-study/.

Risk Summary

ARAVA is contraindicated for use in pregnant women because of the potential for fetal harm. In animal reproduction studies, oral administration of leflunomide during organogenesis at a dose of 1/10 of, and equivalent to, the maximum recommended human dose (MRHD) based on AUC, respectively, in rats and rabbits, caused teratogenicity (rats and rabbits), and embryo-lethality (rats) [see Data]. Pregnancy exposure registry data are not available at this time to inform the presence or absence of drug-associated risk with the use of ARAVA during pregnancy.

The background risk of major birth defects and miscarriage for the indicated populations is unknown. The background risk in the U.S. general population of major birth defects is 2%–4% and of miscarriage is 15%–20% of clinically recognized pregnancies. If this drug is used during pregnancy, or if the patient becomes pregnant while taking this drug, stop treatment with ARAVA, apprise the patient of the potential hazard to a fetus, and perform the accelerated drug elimination procedure to achieve teriflunomide concentrations of less than 0.02 mg/L (0.02 mcg/mL) [see Warnings and Precautions (5.3)].

Clinical Considerations

Fetal/Neonatal adverse reactions

Lowering the plasma concentration of the active metabolite, teriflunomide, by instituting an accelerated drug elimination procedure as soon as pregnancy is detected may decrease the risk to the fetus from ARAVA. The accelerated drug elimination procedure includes verification that the plasma teriflunomide concentration is less than 0.02 mg/L [see Warnings and Precautions (5.3) and Clinical Pharmacology (12.3)].

Data

Animal data

In an embryo-fetal development study, pregnant rats administered leflunomide during organogenesis from gestation days 7 to 19 at a dose approximately 1/10 of the MRHD (on an AUC basis at a maternal oral dose of 15 mg/kg), teratogenic effects, most notably anophthalmia or microphthalmia and internal hydrocephalus, were observed. Under these exposure conditions, leflunomide also caused a decrease in the maternal body weight and an increase in embryolethality with a decrease in fetal body weight for surviving fetuses. In an embryo-fetal development study, pregnant rabbits administered leflunomide during organogenesis from gestation days 6 to 18 at a dose approximately equivalent to the MRHD (on an AUC basis at a maternal oral dose of 10 mg/kg), a teratogenic finding of fused, dysplastic sternebrae was observed. Leflunomide was not teratogenic in rats and rabbits at doses approximately 1/150 and 1/10 of the MRHD, respectively (on an AUC basis at maternal oral dose of 1 mg/kg in both rats and rabbits).

In a pre and postnatal development study, when female rats were treated with leflunomide at a dose that was approximately 1/100 of the MRHD (on an AUC basis at a maternal dose of 1.25 mg/kg) beginning 14 days before mating and continuing until the end of lactation, the offspring exhibited marked (greater than 90%) decreases in postnatal survival.

8.2 Lactation

Risk Summary

Clinical lactation studies have not been conducted to assess the presence of ARAVA in human milk, the effects of ARAVA on the breastfed child, or the effects of ARAVA on milk production. Because of the potential for serious adverse reactions in a breastfed infant from ARAVA, advise a nursing woman to discontinue breastfeeding during treatment with ARAVA.

8.3 Females and Males of Reproductive Potential

ARAVA may cause fetal harm if administered during pregnancy [see Use in Specific Populations (8.1)].

Pregnancy Testing

Exclude pregnancy prior to initiation of treatment with ARAVA in females of reproductive potential. Advise females to notify their healthcare provider immediately if pregnancy occurs or is suspected during treatment [see Warnings and Precautions (5.1, 5.3) and Use in Specific Populations (8.1)].

Contraception

Females

Females of reproductive potential should use effective contraception while taking ARAVA. If ARAVA is discontinued, use of contraception should be continued until it is verified that plasma concentrations of teriflunomide are less than 0.02 mg/L (0.02 mcg/mL, the level expected to have minimal fetal risk, based on animal data).

Females of reproductive potential who wish to become pregnant should discontinue ARAVA and undergo an accelerated elimination procedure. Effective contraception should be used until it is verified that plasma concentrations of teriflunomide are less than 0.02 mg/L (0.02 mcg/mL) [see Warnings and Precautions (5.1, 5.3) and Use in Specific Populations (8.1)].

Males

Teriflunomide, the active metabolite of ARAVA, is detected in human semen. Animal studies to specifically evaluate the risk of male mediated fetal toxicity have not been conducted. To minimize any possible risk, men not wishing to father a child and their female partners should use effective contraception. Men wishing to father a child should discontinue use of ARAVA and either undergo an accelerated elimination procedure or wait until verification that the plasma teriflunomide concentration is less than 0.02 mg/L (0.02 mcg/mL) [see Warnings and Precautions (5.3)].

8.4 Pediatric Use

The safety and effectiveness of ARAVA in pediatric patients have not been established.

The safety and effectiveness of ARAVA in the treatment of polyarticular course juvenile idiopathic arthritis (JIA) was evaluated in a single multicenter, double-blind, active-controlled trial in 94 pediatric patients (1:1 randomization) with polyarticular course juvenile idiopathic arthritis (JIA) as defined by the American College of Rheumatology (ACR). In this population, ARAVA treatment was found not to be effective.

The safety of ARAVA was studied in 74 patients with polyarticular course JIA ranging in age from 3–17 years (47 patients from the active-controlled study and 27 from an open-label safety and pharmacokinetic study). The most common adverse events included abdominal pain, diarrhea, nausea, vomiting, oral ulcers, upper respiratory tract infections, alopecia, rash, headache, and dizziness. Less common adverse events included anemia, hypertension, and weight loss. Fourteen pediatric patients experienced ALT and/or AST elevations, nine between 1.2 and 3-fold the upper limit of normal, and five between 3 and 8-fold the upper limit of normal.

8.5 Geriatric Use

Of the total number of subjects in controlled clinical trials (Trials 1, 2, and 3) of ARAVA, 234 subjects were 65 years and over [see Clinical Studies (14)]. No overall differences in safety or effectiveness were observed between these subjects and younger subjects, and other reported clinical experience has not identified differences in responses between the elderly and younger patients, but greater sensitivity of some older individuals cannot be ruled out. No dosage adjustment is needed in patients over 65.

8.6 Hepatic Impairment

Dedicated studies of the effect of hepatic impairment on leflunomide pharmacokinetics have not been conducted. Given the need to metabolize leflunomide into the active species, the role of the liver in drug elimination/recycling, and the possible risk of increased hepatic toxicity, the use of ARAVA in patients with hepatic impairment is not recommended.

8.7 Renal Impairment

Dedicated studies of the effect of renal impairment on leflunomide pharmacokinetics have not been conducted. Given that the kidney plays an important role in drug elimination, caution should be used when ARAVA is administered to these patients.

10 OVERDOSAGE

There have been reports of chronic overdose in patients taking ARAVA at daily dose up to five times the recommended daily dose and reports of acute overdose in adults and children. Adverse events were consistent with the safety profile for ARAVA [see Adverse Reactions (6)]. The most frequent adverse events observed were diarrhea, abdominal pain, leukopenia, anemia, and elevated liver function tests.

In the event of a significant overdose or toxicity, perform an accelerated drug elimination procedure to accelerate elimination [see Warnings and Precautions (5.3)].

Studies with both hemodialysis and CAPD (chronic ambulatory peritoneal dialysis) indicate that teriflunomide, the primary metabolite of leflunomide, is not dialyzable [see Clinical Pharmacology (12.3)].

11 DESCRIPTION

ARAVA (leflunomide) is a pyrimidine synthesis inhibitor. The chemical name for leflunomide is N-(4´-trifluoromethylphenyl)-5-methylisoxazole-4-carboxamide. It has an empirical formula C12H9F3N2O2, a molecular weight of 270.2 and the following structural formula:

ARAVA is available for oral administration as tablets containing 10, 20, or 100 mg of active drug. Combined with leflunomide are the following inactive ingredients: colloidal silicon dioxide, crospovidone, hypromellose, lactose monohydrate, magnesium stearate, polyethylene glycol, povidone, starch, talc, titanium dioxide, and yellow ferric oxide (20 mg tablet only).

12 CLINICAL PHARMACOLOGY

12.1 Mechanism of Action

Leflunomide is an isoxazole immunomodulatory agent that inhibits dihydroorotate dehydrogenase (a mitochondrial enzyme involved in de novo pyrimidine synthesis) and has antiproliferative activity. Several in vivo and in vitro experimental models have demonstrated an anti-inflammatory effect.

12.3 Pharmacokinetics

Following oral administration, leflunomide is metabolized to an active metabolite, teriflunomide, which is responsible for essentially all of leflunomide's in vivo activity. Plasma concentrations of the parent drug, leflunomide, have been occasionally seen at very low concentrations. Studies of the pharmacokinetics of leflunomide have primarily examined the plasma concentrations of the active metabolite, teriflunomide.

Absorption

Following oral administration, peak teriflunomide concentrations occurred between 6 to 12 hours after dosing. Due to the very long half-life of teriflunomide (18–19 days), a loading dose of 100 mg for 3 days was used in clinical studies to facilitate the rapid attainment of steady-state teriflunomide concentrations. Without a loading dose, it is estimated that attainment of steady-state plasma concentrations would require about two months of dosing. The resulting plasma concentrations following both loading doses and continued clinical dosing indicate that plasma teriflunomide concentrations are dose proportional.

Effect of food

Coadministration of leflunomide tablets with a high fat meal did not have a significant impact on teriflunomide plasma concentrations.

Distribution

Teriflunomide is extensively bound to plasma protein (>99%) and is mainly distributed in plasma. The volume of distribution is 11 L after a single intravenous (IV) administration.

Elimination

Teriflunomide, the active metabolite of leflunomide, has a median half-life of 18 to 19 days in healthy volunteers. The elimination of teriflunomide can be accelerated by administration of cholestyramine or activated charcoal. Without use of an accelerated drug elimination procedure, it may take up to 2 years to reach plasma teriflunomide concentrations of less than 0.02 mg/L, due to individual variation in drug clearance [see Warnings and Precautions (5.3)]. After a single IV administration of the metabolite (teriflunomide), the total body clearance of teriflunomide was 30.5 mL/h.

Metabolism

In vitro inhibition studies in human liver microsomes suggest that cytochrome P450 (CYP) 1A2, 2C19 and 3A4 are involved in leflunomide metabolism. In vivo, leflunomide is metabolized to one primary (teriflunomide) and many minor metabolites. In vitro, teriflunomide is not metabolized by CYP450 or flavin monoamine oxidase enzymes. The parent compound is rarely detectable in plasma.

Excretion

Teriflunomide, the active metabolite of leflunomide, is eliminated by direct biliary excretion of unchanged drug as well as renal excretion of metabolites. Over 21 days, 60.1% of the administered dose is excreted via feces (37.5%) and urine (22.6%). After an accelerated elimination procedure with cholestyramine, an additional 23.1% was recovered (mostly in feces).

Studies with both hemodialysis and CAPD (chronic ambulatory peritoneal dialysis) indicate that teriflunomide is not dialyzable.

Specific Populations

Gender. Gender has not been shown to cause a consistent change in the in vivo pharmacokinetics of teriflunomide.

Smoking. A population based pharmacokinetic analysis of the clinical trial data indicates that smokers have a 38% increase in clearance over nonsmokers; however, no difference in clinical efficacy was seen between smokers and nonsmokers.

Drug Interaction Studies

Drug interaction studies have been conducted with both ARAVA (leflunomide) and with its active metabolite, teriflunomide, where the metabolite was directly administered to the test subjects.

The potential effect of other drugs on ARAVA

- Potent CYP and transporter inducers:

Following concomitant administration of a single dose of ARAVA to subjects receiving multiple doses of rifampin, teriflunomide peak concentrations were increased (~40%) over those seen when ARAVA was given alone [see Drug Interactions (7)].

- An in vivo interaction study with ARAVA and cimetidine (nonspecific weak CYP inhibitor) has demonstrated a lack of a significant impact on teriflunomide exposure.

The potential effect of ARAVA on other drugs

- CYP2C8 Substrates

There was an increase in mean repaglinide Cmax and AUC (1.7 and 2.4-fold, respectively), following repeated doses of teriflunomide and a single dose of 0.25 mg repaglinide, suggesting that teriflunomide is an inhibitor of CYP2C8 in vivo. The magnitude of interaction could be higher at the recommended repaglinide dose [see Drug Interactions (7)].

- CYP1A2 Substrates

Repeated doses of teriflunomide decreased mean Cmax and AUC of caffeine by 18% and 55%, respectively, suggesting that teriflunomide may be a weak inducer of CYP1A2 in vivo.

- OAT3 Substrates

There was an increase in mean cefaclor Cmax and AUC (1.43 and 1.54-fold, respectively), following repeated doses of teriflunomide, suggesting that teriflunomide is an inhibitor of organic anion transporter 3 (OAT3) in vivo [see Drug Interactions (7)].

- BCRP and OATP1B1/1B3 Substrates

There was an increase in mean rosuvastatin Cmax and AUC (2.65 and 2.51-fold, respectively), following repeated doses of teriflunomide, suggesting that teriflunomide is an inhibitor of BCRP transporter and organic anion transporting polypeptide 1B1 and 1B3 (OATP1B1/1B3) [see Drug Interactions (7)].

- Oral Contraceptives

There was an increase in mean ethinylestradiol Cmax and AUC0–24 (1.58 and 1.54-fold, respectively) and levonorgestrel Cmax and AUC0–24 (1.33 and 1.41-fold, respectively) following repeated doses of teriflunomide [see Drug Interactions (7)].

- Teriflunomide did not affect the pharmacokinetics of bupropion (a CYP2B6 substrate), midazolam (a CYP3A4 substrate), S-warfarin (a CYP2C9 substrate), omeprazole (a CYP2C19 substrate), and metoprolol (a CYP2D6 substrate).

13 NONCLINICAL TOXICOLOGY

13.1 Carcinogenesis, Mutagenesis, Impairment of Fertility

No evidence of carcinogenicity was observed in a 2-year bioassay in rats at oral doses of leflunomide up to the maximally tolerated dose of 6 mg/kg (approximately 1/40 the maximum human teriflunomide systemic exposure based on AUC). However, male mice in a 2-year bioassay exhibited an increased incidence in lymphoma at an oral dose of 15 mg/kg, the highest dose studied (1.7 times the human teriflunomide exposure based on AUC). Female mice, in the same study, exhibited a dose-related increased incidence of bronchoalveolar adenomas and carcinomas combined beginning at 1.5 mg/kg (approximately 1/10 the human teriflunomide exposure based on AUC). The significance of the findings in mice relative to the clinical use of ARAVA is not known.

Leflunomide was not mutagenic in the Ames assay, the unscheduled DNA synthesis assay, or in the HGPRT gene mutation assay. In addition, leflunomide was not clastogenic in the in vivo mouse micronucleus assay or in the in vivo Chinese hamster bone marrow cell cytogenic test. However, 4-trifluoromethylaniline (TFMA), a minor metabolite of leflunomide, was mutagenic in the Ames assay and in the HGPRT gene mutation assay, and was clastogenic in the in vitro Chinese hamster cell chromosomal aberration assay. TFMA was not clastogenic in the in vivo mouse micronucleus assay or in the in vivo Chinese hamster bone marrow cell cytogenic test.

Leflunomide had no effect on fertility or reproductive performance in either male or female rats at oral doses up to 4.0 mg/kg (approximately 1/30 the human teriflunomide exposure based on AUC) [see Use in Specific Populations (8.1, 8.6)].

14 CLINICAL STUDIES

The efficacy of ARAVA in the treatment of rheumatoid arthritis (RA) was demonstrated in three controlled trials showing reduction in signs and symptoms, and inhibition of structural damage. In two placebo-controlled trials, efficacy was demonstrated for improvement in physical function. In these trials, efficacy was evaluated by:

1. Reduction of signs and symptoms
  Relief of signs and symptoms was assessed using the American College of Rheumatology (ACR) 20 Responder Index, a composite of clinical, laboratory, and functional measures in rheumatoid arthritis. An "ACR20 Responder" is a patient who had ≥20% improvement in both tender and swollen joint counts and in 3 of the following 5 criteria: physician global assessment, patient global assessment, functional ability measure (Modified Health Assessment Questionnaire [MHAQ]), visual analog pain scale, and erythrocyte sedimentation rate or C-reactive protein. An "ACR20 Responder at Endpoint" is a patient who completed the study and was an ACR20 Responder at the completion of the study.
2. Inhibition of structural damage
  Inhibition of structural damage compared to control was assessed using the Sharp score, a composite score of x-ray erosions and joint space narrowing in hands/wrists and forefeet.
3. Improvement in physical function
  Improvement in physical function was assessed using the Health Assessment Questionnaire (HAQ) and the Medical Outcomes Survey Short Form (SF-36).
  In all ARAVA trials, participants of at least 18 years of age and in ARA functional class of I, II, or III received an initial loading dose of 100 mg leflunomide per day for three days, followed by 20 mg per day thereafter.
  Exclusion criteria included patients with a history of hypersensitivity to the study medication; women who were pregnant or breastfeeding and men or women of child bearing age and potential who had not received contraceptives for at least 4 weeks before entering the study and to be maintained throughout the study and for at least 6 months after discontinuing treatment; patients with a history of inflammatory disease, impaired renal function or liver impairment, cardiac failure, congenital or acquired immunodeficiency, impaired coagulation, or a history of recent major traumatic injury; and patients taking intra-articular or systemic concomitant medications which could affect the safety and/or efficacy of the study medication.

Trial 1

Trial 1, a 2-year study, randomized 482 patients with active RA of at least 6 months duration to leflunomide 20 mg/day (n=182), methotrexate 7.5 mg/week increasing to 15 mg/week (n=182), or placebo (n=118). All patients received folate 1 mg BID. The primary analysis was at 52 weeks with blinded treatment to 104 weeks.

Overall, 235 of the 508 randomized treated patients (482 in primary data analysis and an additional 26 patients), continued into a second 12 months of double-blind treatment (98 leflunomide, 101 methotrexate, 36 placebo). Leflunomide dose continued at 20 mg/day and the methotrexate dose could be increased to a maximum of 20 mg/week. In total, 190 patients (83 leflunomide, 80 methotrexate, 27 placebo) completed 2 years of double-blind treatment.

Trial 2

Trial 2 randomized 358 patients with active RA to leflunomide 20 mg/day (n=133), sulfasalazine 2.0 g/day (n=133), or placebo (n=92). Treatment duration was 24 weeks. An extension of the study was an optional 6-month blinded continuation of Trial 2 without the placebo arm, resulting in a 12-month comparison of leflunomide and sulfasalazine.

Of the 168 patients who completed 12 months of treatment, 146 patients (87%) entered a 1-year extension study of double-blind active treatment; (60 leflunomide, 60 sulfasalazine, 26 placebo/sulfasalazine). Patients continued on the same daily dosage of leflunomide or sulfasalazine that they had been taking at the completion of Trial 2. A total of 121 patients (53 leflunomide, 47 sulfasalazine, 21 placebo/sulfasalazine) completed the 2 years of double-blind treatment.

Trial 3

Trial 3 randomized 999 patients with active RA to leflunomide 20 mg/day (n=501) or methotrexate at 7.5 mg/week increasing to 15 mg/week (n=498). Folate supplementation was used in 10% of patients. Treatment duration was 52 weeks.

Of the 736 patients who completed 52 weeks of treatment in study Trial 3, 612 (83%) entered the double-blind, 1-year extension study (292 leflunomide, 320 methotrexate). Patients continued on the same daily dosage of leflunomide or methotrexate that they had been taking at the completion of Trial 3. There were 533 patients (256 leflunomide, 277 methotrexate) who completed 2 years of double-blind treatment.

Clinical Trial Results

Clinical response

The ACR20 Responder at Endpoint rates are shown in Figure 1. ARAVA was statistically significantly superior to placebo in reducing the signs and symptoms of RA by the primary efficacy analysis, ACR20 Responder at Endpoint, in study Trial 1 (at the primary 12 months endpoint) and Trial 2 (at 6-month endpoint). ACR20 Responder at Endpoint rates with ARAVA treatment were consistent across the 6 and 12-month studies (41%–49%). No consistent differences were demonstrated between leflunomide and methotrexate or between leflunomide and sulfasalazine. ARAVA treatment effect was evident by 1 month, stabilized by 3 to 6 months, and continued throughout the course of treatment as shown in Figure 1.

Figure 1: Percentage of ACR20 Responders at Endpoint in Patients with Active RA in Trials 1, 2, and 3

 | Comparisons | 95% Confidence Interval | p Value
Trial 1 | ARAVA vs Placebo | (12, 32) | <0.0001
 | Methotrexate vs Placebo | (8, 30) | <0.0001
 | ARAVA vs Methotrexate | (-4, 16) | NS
Trial 2 | ARAVA vs Placebo | (7, 33) | 0.0026
 | Sulfasalazine vs Placebo | (4, 29) | 0.0121
 | ARAVA vs Sulfasalazine | (-8, 16) | NS
Trial 3 | ARAVA vs Methotrexate | (-19, -7) | <0.0001

Figure 2: ACR20 Responders over Time in Patients with Active RA in Trial 1*

ACR50 and ACR70 Responders are defined in an analogous manner to the ACR 20 Responder, but use improvements of 50% or 70%, respectively (Table 3). Mean change for the individual components of the ACR Responder Index are shown in Table 4.

Table 3: Summary of ACR Response Rates in Patients with Active RA in Trials 1, 2, and 3 [Intent to treat (ITT) analysis using last observation carried forward (LOCF) technique for patients who discontinued early.]
Study and Treatment Group | ACR20 | ACR50 | ACR70
Placebo-Controlled Studies
Trial 1 (12 months)
ARAVA (n=178) [n is the number of ITT patients for whom adequate data were available to calculate the indicated rates.] | 52 [p<0.001 ARAVA vs placebo] | 34 | 20
Placebo (n=118) | 26 | 8 | 4
Methotrexate (n=180) | 46 | 23 | 9
Trial 2 (6 months)
ARAVA (n=130) | 55 | 33 | 10 [p<0.02 ARAVA vs placebo]
Placebo (n=91) | 29 | 14 | 2
Sulfasalazine (n=132) | 57 | 30 | 8
Non-Placebo Active-Controlled Studies
Trial 3 (12 months)
ARAVA (n=495) | 51 | 31 | 10
Methotrexate (n=489) | 65 | 44 | 16

Table 4 shows the results of the components of the ACR response criteria for Trial 1, Trial 2, and Trial 3. ARAVA was significantly superior to placebo in all components of the ACR Response criteria in study Trial 1 and Trial 2. In addition, ARAVA was significantly superior to placebo in improving morning stiffness, a measure of RA disease activity, not included in the ACR Response criteria. No consistent differences were demonstrated between ARAVA and the active comparators.

Table 4: Mean Change in the Components of the ACR Responder Index in Patients with Active RA in Trials 1, 2, and 3 [Last Observation Carried Forward; Negative Change Indicates Improvement]
Components | Placebo-Controlled Studies |  |  |  |  |  | Non–Placebo-Controlled Study
 | Trial 1 (12 months) |  |  | Trial 2 Non-US (6 months) |  |  | Trial 3 Non-US (12 months)
 | Leflunomide | Methotrexate | Placebo | Leflunomide | Sulfasalazine | Placebo | Leflunomide | Methotrexate
Tender joint count [Based on 28 joint count] | -7.7 | -6.6 | -3.0 | -9.7 | -8.1 | -4.3 | -8.3 | -9.7
Swollen joint count | -5.7 | -5.4 | -2.9 | -7.2 | -6.2 | -3.4 | -6.8 | -9.0
Patient global assessment [Visual Analog Scale - 0=Best; 10=Worst] | -2.1 | -1.5 | 0.1 | -2.8 | -2.6 | -0.9 | -2.3 | -3.0
Physician global assessment | -2.8 | -2.4 | -1.0 | -2.7 | -2.5 | -0.8 | -2.3 | -3.1
Physical function/disability (MHAQ/HAQ) | -0.29 | -0.15 | 0.07 | -0.50 | -0.29 | -0.04 | -0.37 | -0.44
Pain intensity | -2.2 | -1.7 | -0.5 | -2.7 | -2.0 | -0.9 | -2.1 | -2.9
Erythrocyte Sedimentation rate | -6.26 | -6.48 | 2.56 | -7.48 | -16.56 | 3.44 | -10.12 | -22.18
C-reactive protein | -0.62 | -0.50 | 0.47 | -2.26 | -1.19 | 0.16 | -1.86 | -2.45
Not included in the ACR Responder Index
Morning Stiffness (min) | -101.4 | -88.7 | 14.7 | -93.0 | -42.4 | -6.8 | -63.7 | -86.6

Maintenance of effect

After completing 12 months of treatment, patients continuing on study treatment were evaluated for an additional 12 months of double-blind treatment (total treatment period of 2 years). ACR Responder rates at 12 months were maintained over 2 years in most patients continuing a second year of treatment.

Improvement from baseline in the individual components of the ACR responder criteria was also sustained in most patients during the second year of ARAVA treatment in all three trials.

Radiographic Response

The change from baseline to endpoint in progression of structural disease, as measured by the Sharp x-ray score, is displayed in Figure 3. ARAVA was statistically significantly superior to placebo in inhibiting the progression of disease by the Sharp score. No consistent differences were demonstrated between leflunomide and methotrexate or between leflunomide and sulfasalazine.

Figure 3: Change in Sharp Score in Patients with Active RA in Trials 1, 2, and 3

Comparisons |  | 95% Confidence Interval | p Value
Trial 1 | ARAVA vs Placebo | (-4.0, -1.1) | 0.0007
Trial 1 | Methotrexate vs Placebo | (-2.6, -0.2) | 0.0196
 | ARAVA vs Methotrexate | (-2.3, 0.0) | 0.0499
Trial 2 | ARAVA vs Placebo | (-6.2, -1.8) | 0.0004
Trial 2 | Sulfasalazine vs Placebo | (-6.9, 0.0) | 0.0484
Trial 2 | ARAVA vs Sulfasalazine | (-3.3, 1.2) | NS
Trial 3 | ARAVA vs Methotrexate | (-2.2, 7.4) | NS

Physical Function Response

The Health Assessment Questionnaire (HAQ) assesses a patient's physical function and degree of disability. The mean change from baseline in functional ability as measured by the HAQ Disability Index (HAQ DI) in the 6 and 12-month placebo and active-controlled trials is shown in Figure 4. ARAVA was statistically significantly superior to placebo in improving physical function. Superiority to placebo was demonstrated consistently across all eight HAQ DI subscales (dressing, arising, eating, walking, hygiene, reach, grip, and activities) in both placebo-controlled studies.

The Medical Outcomes Survey Short Form 36 (SF-36), a generic health-related quality of life questionnaire, further addresses physical function. In Trial 1, at 12 months, ARAVA provided statistically significant improvements compared to placebo in the Physical Component Summary (PCS) Score.

Figure 4: Change in Functional Ability Measure in Patients with Active RA in Trials 1, 2, and 3*

Comparison |  | 95% Confidence Interval | p Value
Trial 1 | ARAVA vs Placebo | (-0.58, -0.29) | 0.0001
Trial 1 | ARAVA vs Methotrexate | (-0.34, -0.07) | 0.0026
Trial 2 | ARAVA vs Placebo | (-0.67, -0.36) | <0.0001
Trial 2 | ARAVA vs Sulfasalazine | (-0.33, -0.03) | 0.0163
Trial 3 | ARAVA vs Methotrexate | (0.01, 0.16) | 0.0221

Maintenance of effect

The improvement in physical function demonstrated at 6 and 12 months was maintained over two years. In those patients continuing therapy for a second year, this improvement in physical function as measured by HAQ and SF-36 (PCS) was maintained.

16 HOW SUPPLIED/STORAGE AND HANDLING

How Supplied

ARAVA (leflunomide) Tablets

Strength | Quantity | NDC Number | Description
10 mg | 30 count bottle | 0088-2160-30 | White, round film-coated tablet embossed with "ZBN" on one side.
20 mg | 30 count bottle | 0088-2161-30 | Light yellow, triangular film-coated tablet embossed with "ZBO" on one side.
100 mg | 3 count blister pack | 0088-2162-33 | White, round film-coated tablet embossed with "ZBP" on one side.

STORAGE AND HANDLING

Store at 25°C (77°F); excursions permitted to 15°C to 30°C (59°F to 86°F) [see USP Controlled Room Temperature]. Protect from light.

17 PATIENT COUNSELING INFORMATION

Embryo-Fetal Toxicity

Advise females of reproductive potential:

- Of the potential for fetal harm if ARAVA is taken during pregnancy.
- To notify their healthcare provider immediately if a pregnancy occurs or is suspected.
- To use effective contraception during treatment with ARAVA and until the active metabolite (teriflunomide) plasma concentration is verified to be less than 0.02 mg/L [see Warnings and Precautions (5.1, 5.3), Use in Specific Populations (8.1, 8.3), and Clinical Pharmacology (12.3)].

Pregnancy Exposure Registry

There is a pregnancy exposure registry that monitors pregnancy outcomes in women exposed to ARAVA during pregnancy [see Use in Specific Populations (8.1)].

Lactation

Advise nursing women to discontinue breastfeeding during treatment with ARAVA [see Use in Specific Populations (8.2)].

Serious Skin Reactions

Advise patients of the possibility of rare, serious skin reactions. Instruct patients to promptly seek medical attention if they develop a skin rash, mucous membrane lesions, or skin ulcers.

Investigations

- Advise patients of the potential hepatotoxic effects of ARAVA and of the need for monitoring liver enzymes. Instruct patients to report if they develop symptoms such as unusual tiredness, abdominal pain or jaundice.
- Advise patients that they may develop a lowering of their blood counts and should have frequent hematologic monitoring. This is particularly important for patients who are receiving other immunosuppressive therapy concurrently with ARAVA, who have recently discontinued such therapy before starting treatment with ARAVA, or who have had a history of a significant hematologic abnormality. Instruct patients to promptly report if they notice symptoms consistent with pancytopenia, such as easy bruising or bleeding, recurrent infections, fever, paleness or unusual tiredness.
- Inform patients about the early warning signs of interstitial lung disease and ask them to contact their physician promptly if these symptoms appear or worsen during therapy.

sanofi-aventis U.S. LLC
Morristown, NJ 07960
A SANOFI COMPANY
©2025 sanofi-aventis U.S. LLC

PRINCIPAL DISPLAY PANEL - 10 mg Carton

NDC 0088-2160-30

Arava®
Tablets

leflunomide

10mg

OVERSIZED CONTAINER
FOR EASE OF PATIENT USE

30 Tablets

sanofi aventis

PRINCIPAL DISPLAY PANEL - 20 mg Carton

NDC 0088-2161-30

Arava®
Tablets

leflunomide

20mg

OVERSIZED CONTAINER
FOR EASE OF PATIENT USE

30 Tablets

sanofi aventis

PRINCIPAL DISPLAY PANEL - 100 mg Carton

0088-2162-33
Rx Only

Arava®
Tablets

leflunomide

100mg

Initiation-Dose Kit
PHYSICIAN SAMPLE - NOT TO BE SOLD

Remember: Have your Arava® prescription filled
before you take the tablets in this package.

Please see enclosed additional important information.

Contains three 100-mg tablets

sanofi aventis